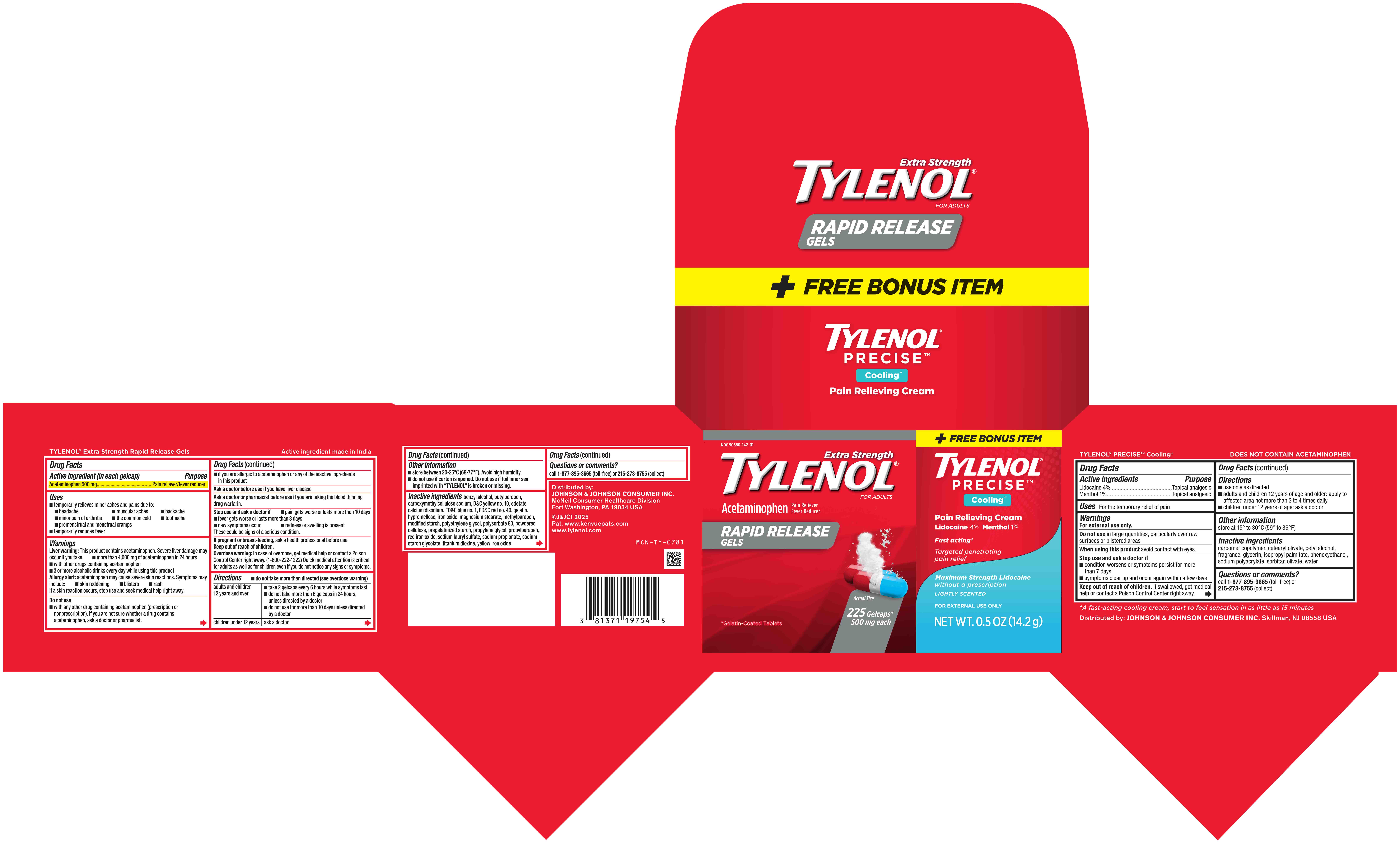 DRUG LABEL: TYLENOL Extra Strength / TYLENOL Precise Cooling Pain Relief
NDC: 50580-142 | Form: KIT | Route: ORAL
Manufacturer: Kenvue Brands LLC
Category: otc | Type: HUMAN OTC DRUG LABEL
Date: 20241126

ACTIVE INGREDIENTS: ACETAMINOPHEN 500 mg/1 1; LIDOCAINE 40 mg/1 g; MENTHOL, UNSPECIFIED FORM 10 mg/1 g
INACTIVE INGREDIENTS: FD&C RED NO. 40; MAGNESIUM STEARATE; POLYETHYLENE GLYCOL, UNSPECIFIED; POLYSORBATE 80; CARBOXYMETHYLCELLULOSE SODIUM, UNSPECIFIED; FD&C BLUE NO. 1; FERRIC OXIDE YELLOW; POWDERED CELLULOSE; PROPYLENE GLYCOL; D&C YELLOW NO. 10; SODIUM LAURYL SULFATE; BUTYLPARABEN; GELATIN, UNSPECIFIED; EDETATE CALCIUM DISODIUM; HYPROMELLOSE, UNSPECIFIED; TITANIUM DIOXIDE; FERRIC OXIDE RED; FERROSOFERRIC OXIDE; BENZYL ALCOHOL; METHYLPARABEN; PROPYLPARABEN; SODIUM PROPIONATE; SODIUM STARCH GLYCOLATE TYPE A; PHENOXYETHANOL; SORBITAN OLIVATE; GLYCERIN; CETEARYL OLIVATE; WATER; SODIUM POLYACRYLATE (2500000 MW); ISOPROPYL PALMITATE; CETYL ALCOHOL

TYLENOL® EXTRA STRENGHT / TYLENOL® PRECISE COOLING PAIN RELIEF

Drug Facts

Active ingredient (in each gelcap)

Acetaminophen 500 mg

Purpose

Pain reliever/fever reducer

Uses

■ temporarily relieves minor aches and pains due to:

- headache
- muscular aches
- backache
- minor pain of arthritis
- the common cold
- toothache
- premenstrual and menstrual cramps

■ temporarily reduces fever

Warnings

Liver warning

This product contains acetaminophen. Severe liver damage may occur if you take

■ more than 4,000 mg of acetaminophen in 24 hours
■ with other drugs containing acetaminophen
■ 3 or more alcoholic drinks every day while using this product

Allergy alert: acetaminophen may cause severe skin reactions. Symptoms may include:

- skin reddening
- blisters
- rash

If a skin reaction occurs, stop use and seek medical help right away.

Do not use

■ with any other drug containing acetaminophen (prescription or nonprescription). If you are not sure whether a drug contains
acetaminophen, ask a doctor or pharmacist.

■ if you are allergic to acetaminophen or any of the inactive ingredients in this product

Ask a doctor before use if you have liver disease

Ask a doctor or pharmacist before use if you are taking the blood thinning drug warfarin.

Stop use and ask a doctor if

■ pain gets worse or lasts more than 10 days
■ fever gets worse or lasts more than 3 days
■ new symptoms occur

■ redness or swelling is present

These could be signs of a serious condition.

PREGNANCY OR BREAST FEEDING

If pregnant or breast-feeding, ask a health professional before use.

Keep out of reach of children.

Overdose warning

In case of overdose, get medical help or contact a Poison Control Center right away. (1-800-222-1222) Quick medical attention is critical for adults as well as for children even if you do not notice any signs or symptoms.

Directions

- do not take more than directed (see overdose warning)

adults and children 12 years and over | ■ take 2 gelcaps every 6 hours while symptoms last ■ do not take more than 6 gelcaps in 24 hours, unless directed by a doctor ■ do not use for more than 10 days unless directed by a doctor
children under 12 years | ask a doctor

Other information

■ store between 20-25°C (68-77°F). Avoid high humidity.
■ do not use if carton is opened. Do not use if foil inner seal imprinted with “TYLENOL” is broken or missing.

Inactive ingredients

benzyl alcohol, butylparaben, carboxymethylcellulose sodium, D&C yellow no. 10, edetate calcium disodium, FD&C blue no. 1, FD&C red no. 40, gelatin, hypromellose, iron oxide, magnesium stearate, methylparaben, modified starch, polyethylene glycol, polysorbate 80, powdered cellulose, pregelatinized starch, propylene glycol, propylparaben, red iron oxide, sodium lauryl sulfate, sodium propionate, sodium starch glycolate, titanium dioxide, yellow iron oxide

Questions or comments?

call 1-877-895-3665 (toll-free) or 215-273-8755 (collect)

Active Ingredient

Lidocaine 4%

Menthol 1%

Purpose

Topical analgesic

Topical analgesic

Uses

For the temporary relief of pain

Warnings

For external use only.

Do not use

▪ in large quantities, particularly over raw surfaces or blistered areas

When using this product

▪ avoid contact with eyes

Stop use and ask a doctor if

▪ condition worsens or symptoms persist for more than 7 days

▪ symptoms clear up and occur again within a few days

Keep out of reach of children. If swallowed, get medical help or contact a Poison Control Center right away.

Directions

■ use only as directed
■ adults and children 12 years of age and older: apply to affected area not more than 3 to 4 times daily
■ children under 12 years of age: ask a doctor

Other Information

store at 15◦ to 30◦ C (59◦ to 86◦ F)

Inactive Ingredients

carbomer copolymer, cetearyl olivate, cetyl alcohol, fragrance, glycerin, isopropyl palmitate, phenoxyethanol, sodium polyacrylate, sorbitan olivate, water

Questions?

Call 1-877-895-3665 (toll-free) or 215- 273-8755 (collect)

PRINCIPAL DISPLAY PANEL

NDC 50580-142-01

Extra Strength

TYLENOL®

FOR ADULTS

Acetaminophen
Pain Reliever
Fever Reducer

RAPID RELEASE GELS

Actual Size

225 Gelcaps*
500 mg each

*Gelatin-Coated Tablets

+ FREE BONUS ITEM

TYLENOL®

PRECISETM

Cooling†

Pain Relieving Cream

Lidocaine 4% Menthol 1%

Fast acting†

Targeted penetrating

pain relief

Maximum Strength Lidocaine

without a prescription

LIGHTLY SCENTED

For external use only

NET WT. 0.5 OZ (14.2 g)